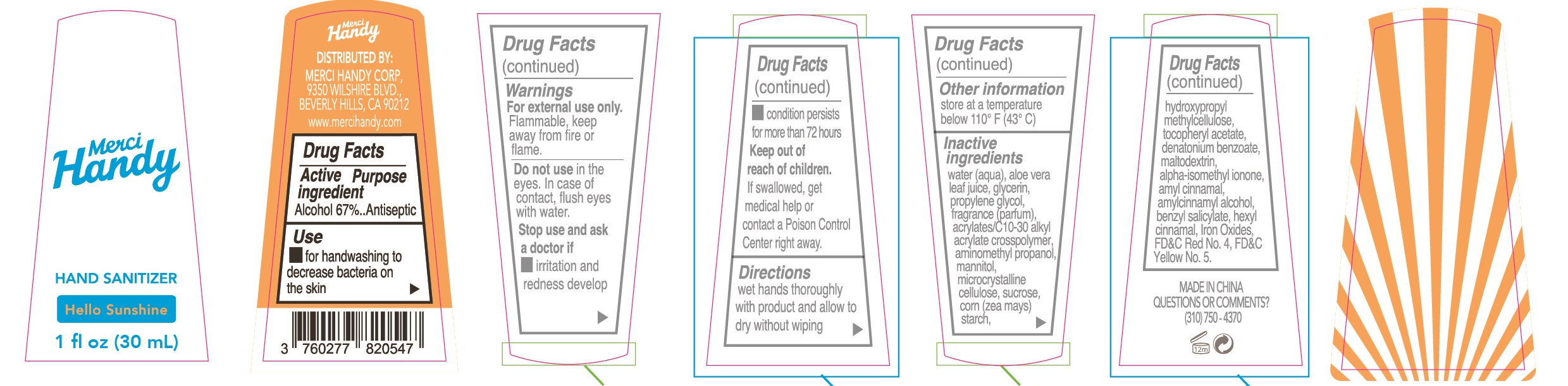 DRUG LABEL: Hand Sanitizer
NDC: 72866-103 | Form: GEL
Manufacturer: Merci Handy Corporation
Category: otc | Type: HUMAN OTC DRUG LABEL
Date: 20190223

ACTIVE INGREDIENTS: ALCOHOL 67 mL/100 mL
INACTIVE INGREDIENTS: .ALPHA.-HEXYLCINNAMALDEHYDE; .ALPHA.-IONONE; BENZYL SALICYLATE; DENATONIUM BENZOATE; MALTODEXTRIN; .ALPHA.-AMYLCINNAMALDEHYDE; PROPYLENE GLYCOL; MANNITOL; WATER; ALOE VERA LEAF; GLYCERIN; CARBOMER INTERPOLYMER TYPE A (55000 CPS); AMINOMETHYLPROPANOL; CELLULOSE, MICROCRYSTALLINE; SUCROSE; STARCH, CORN; .ALPHA.-TOCOPHEROL ACETATE; HYPROMELLOSES; FD&C RED NO. 4; FD&C YELLOW NO. 5; .ALPHA.-AMYLCINNAMYL ALCOHOL; BROWN IRON OXIDE

Active ingredient
Alcohol 67%

Purpose
Antiseptic

Uses

for handwashing to decrease bacteria on the skin.

Warnings

For external use only. Flammable, keep away from fire or flame.

Do not use in the eyes.In case of contact, flush eyes with water.

Stop use and ask a doctor if

- irritation and redness develop.
- condition persists for more than 72 hours

Keep out of reach of children. If swallowed, get medical help or contact a Poison Control Center right away.

Directions

wet hand thoroughly with product and allow to dry without wiping

Other information

store at a temperature below 110 F(43 C)

Inactive ingredients

water(aqua), aloe vera leaf juice, glycerin, propylene glycol, fragrance(parfum), acrylates/C30-10 alkyl acrylate crosspolymer, aminomethyl propanol, mannitol, microcrystalline cellulose, sucrose, corn(zea mays) starch, hydroxpropyl methyl cellulose, tocopheryl acetate, denatonium benzonate, maltodextrin, alpha-isomethyl ionone, amyl cinnamal, amylcinnamyl alcohol, benzyl salicylate, hexyl cinnamal, Iron Oxides, FD&C Red No.4, FD&C Yellow No.5.